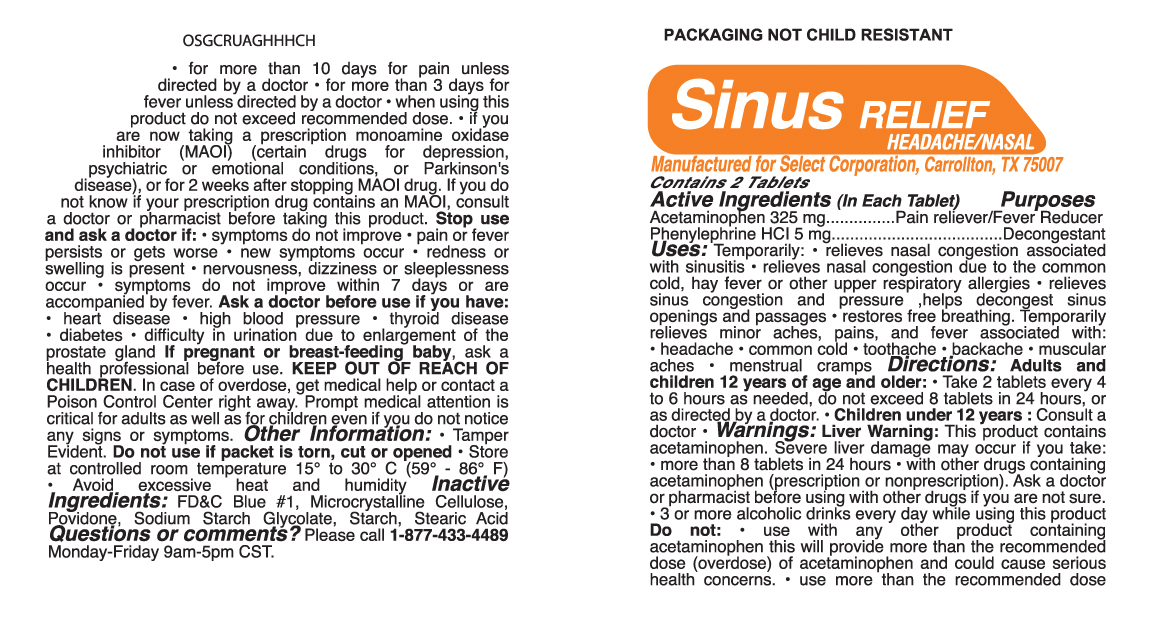 DRUG LABEL: Sinus Relief Headache Nasal
                
NDC: 52904-493 | Form: TABLET
Manufacturer: Select Corporation
Category: otc | Type: HUMAN OTC DRUG LABEL
Date: 20121015

ACTIVE INGREDIENTS: ACETAMINOPHEN 325 mg/1 1; PHENYLEPHRINE HYDROCHLORIDE 5 mg/1 1
INACTIVE INGREDIENTS: STARCH, CORN; POVIDONE K30; STEARIC ACID; CELLULOSE, MICROCRYSTALLINE; SODIUM STARCH GLYCOLATE TYPE A POTATO; FD&C BLUE NO. 1

Drug Facts

Active Ingredients

Acetaminophen 325 mg.......................Pain Reliever/Fever Reducer
Phenylephrine HCl 5 mg.............................Nasal Decongestant

PURPOSE

Pain Reliever, Fever Reducer, Nasal Decongestant

DOSAGE AND ADMINISTRATION

Directions: Adults and children 12 years of age and older: • Take 2 tablets every 4
to 6 hours as needed, do not exceed 8 tablets in 24 hours, or
as directed by a doctor. • Children under 12 years : Consult a
doctor

INDICATIONS AND USAGE

Uses: Temporarily: • relieves nasal congestion associated
with sinusitis • relieves nasal congestion due to the common
cold, hay fever or other upper respiratory allergies • relieves
sinus congestion and pressure ,helps decongest sinus
openings and passages • restores free breathing. Temporarily
relieves minor aches, pains, and fever associated with:
• headache • common cold • toothache • backache • muscular
aches • menstrual cramps

Warnings: Liver Warning: This product contains
acetaminophen. Severe liver damage may occur if you take:
• more than 8 tablets in 24 hours • with other drugs containing
acetaminophen (prescription or nonprescription). Ask a doctor
or pharmacist before using with other drugs if you are not sure.
• 3 or more alcoholic drinks every day while using this product
Do not: • use with any other product containing
acetaminophen this will provide more than the recommended
dose (overdose) of acetaminophen and could cause serious
health concerns. • use more than the recommended dose
for more than 10 days for pain unless
directed by a doctor • for more than 3 days for
fever unless directed by a doctor • when using this
product do not exceed recommended dose. • if you
are now taking a prescription monoamine oxidase
inhibitor (MAOI) (certain drugs for depression,
psychiatric or emotional conditions, or Parkinson's
disease), or for 2 weeks after stopping MAOI drug. If you do
not know if your prescription drug contains an MAOI, consult
a doctor or pharmacist before taking this product. Stop use
and ask a doctor if: • symptoms do not improve • pain or fever
persists or gets worse • new symptoms occur • redness or
swelling is present • nervousness, dizziness or sleeplessness
occur • symptoms do not improve within 7 days or are
accompanied by fever. Ask a doctor before use if you have:
• heart disease • high blood pressure • thyroid disease
• diabetes • difficulty in urination due to enlargement of the
prostate gland

PREGNANCY OR BREAST FEEDING

If pregnant or breast-feeding baby, ask a health professional
before use.

KEEP OUT OF REACH OF CHILDREN.

Inactive Ingredients: corn starch, FDC Blue 1, maltodextrin,
microcrystalline cellulose, polyethylene glycol, povidone, sodium
starch glycolate, and stearic acid

PACKAGE LABEL

MM1